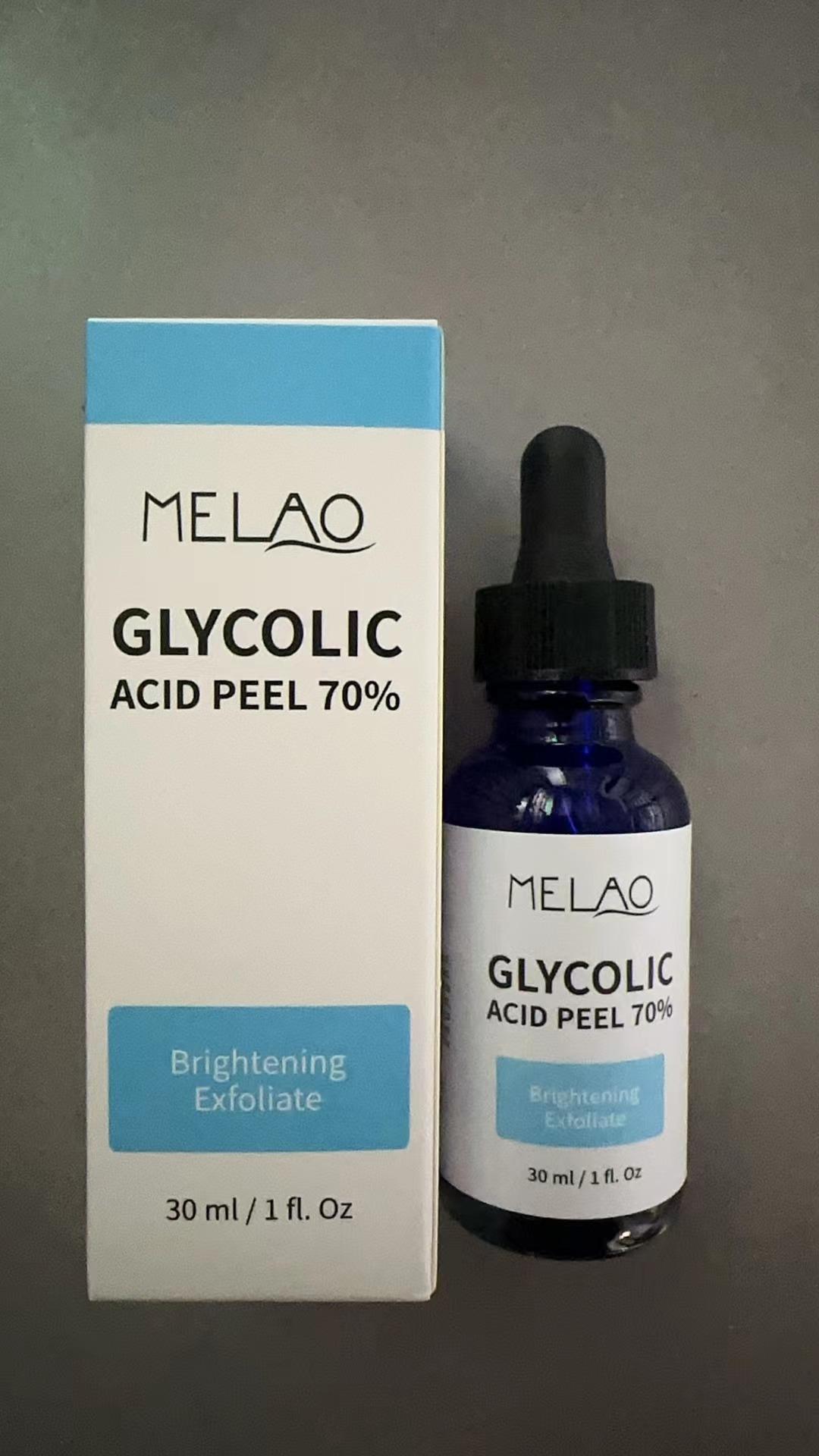 DRUG LABEL: MELAO GLYCOLIC ACID PEEL 70%
NDC: 83566-570 | Form: LIQUID
Manufacturer: Guangzhou Yilong Cosmetics Co., Ltd
Category: otc | Type: HUMAN OTC DRUG LABEL
Date: 20240807

ACTIVE INGREDIENTS: GLYCERIN 4 g/100 g; DIPOTASSIUM GLUCARATE 2 g/100 g
INACTIVE INGREDIENTS: WATER O-18 60 g/100 g; ALLANTOIN BIOTIN 3 g/100 g; PEG-9 DIGLYCIDYL ETHER/SODIUM HYALURONATE CROSSPOLYMER 4 g/100 g; BUTYLENE GLYCOL 15 g/100 g; DIPROPYLENE GLYCOL CAPRYLATE 5 g/100 g

Active ingredients

Dipotassium Glycyrrhizate 2%

Glycerin4%

Inactive ingredients

Water 60%

Butylene Glycol15%

Propylene Glycol5%

Sodium Hyaluronate4%

Allantoin3%

Panthenol2%

Xanthan Gum2%

Dipotassium Glycyrrhizate2%

Glyceryl Polymetha crylate2%

Saccharum Officinarum (Sugarcane) Extract0.5%

Fragrance0.5%

Purpose

Moisture

Uses

Step 1: Clean and thoroughly dry your skin.
Step 2: Rotate the bottle cap to open the product.
Step 3: Gently apply to the surface of the skin.

Warnings

For external use only.

Stop use and ask a doctor if

rash occurs.

Do not use

on damaged or broken skin.

When using this product

keep out of eyes. Rinse withwater to remove.

Keep out of reach of children.

DOSAGE & ADMINISTRATION

Squeeze out an appropriate amount of sunscreen and spread evenly on skin.